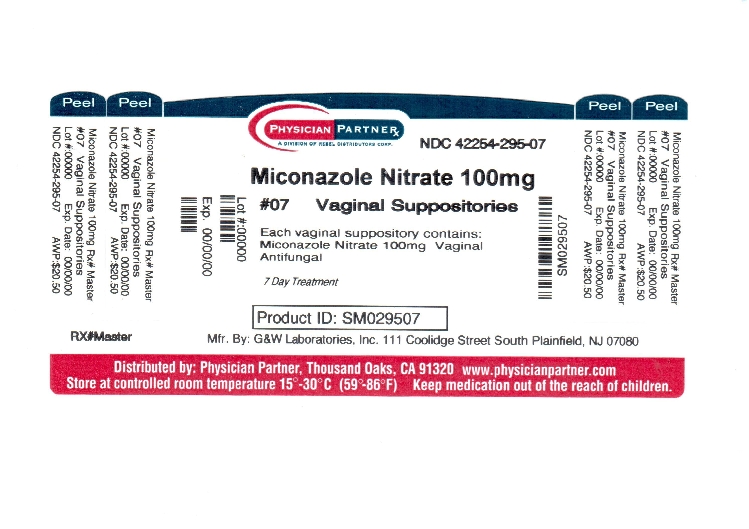 DRUG LABEL: Miconazole Nitrate
NDC: 42254-295 | Form: SUPPOSITORY
Manufacturer: Rebel Distributors Corp
Category: otc | Type: HUMAN OTC DRUG LABEL
Date: 20120926

ACTIVE INGREDIENTS: Miconazole Nitrate 100 ug/1 1
INACTIVE INGREDIENTS: Hydrogenated Coconut Oil

Miconazole Nitrate, Vaginal Suppositories USP, 100 mg

OTC - ACTIVE INGREDIENT SECTION

Miconazole nitrate 100 mg

OTC - PURPOSE SECTION

Vaginal Antifungal

INDICATIONS & USAGE SECTION

Use
• treats vaginal yeast infections

WARNINGS SECTION

WARNINGS
For vaginal use only
Do not use if you have never had a vaginal yeast infection diagnosed by a doctor
Ask a doctor before use if you have
• vaginal itching and discomfort for the first time
• lower abdominal, back or shoulder pain, fever, chills, nausea, vomiting, or foul-smelling vaginal discharge
• vaginal yeast infections often (such as once a month or 3 in 6 months). You could be pregnant or have a serious underlying medical cause for your symptoms, including diabetes or a weakened immune system.
• been exposed to the human immunodeficiency virus (HIV) that causes AIDS
Ask a doctor or pharmacist before use if you are taking the prescription blood thinning medicine warfarin, because bleeding or bruising may occur.
When using this product
• do not use tampons, douches, spermicides, or other vaginal products. Condoms and diaphragms may be damaged by this product and fail to prevent pregnancy or sexually transmitted diseases (STDs).
• do not have vaginal intercourse
Stop use and ask a doctor if
• symptoms do not get better in 3 days
• symptoms last more than 7 days
• you get a rash, abdominal pain, fever, chills, nausea, vomiting, or foul-smelling vaginal discharge
• In case of accidental ingestion, seek professional assistance or contact a poison control center immediately.

OTC - PREGNANCY OR BREAST FEEDING SECTION

If pregnant or breast-feeding, ask a health professional before use

OTC - KEEP OUT OF REACH OF CHILDREN SECTION

Keep out of reach of children. If swallowed, get medical help or contact a Poison Control Center right away.

DOSAGE & ADMINISTRATION SECTION

Directions
• before using this product, read the enclosed brochure for complete instructions
• adults and children 12 years of age and over:
• insert 1 suppository into the vagina at bedtime for 7 nights in a row
• wash applicator after each use
• children under 12 years of age: ask a doctor

STORAGE AND HANDLING SECTION

• store at 15°-30°C (59°-86°F). Avoid heat over 30°C (86°F).
• do not use if suppository wrapper is missing or damaged (each suppository is individually wrapped)

INACTIVE INGREDIENT SECTION

hydrogenated vegetable oil base

OTC - QUESTIONS SECTION

QUESTION?
call 1-800-922-1038

PACKAGE LABEL.PRINCIPAL DISPLAY PANEL

Miconazole Nitrate Vaginal Suppositories USP, 100 mg
NDC 42254-295-07
7 Day Treatment
Miconazole Nitrate Vaginal Suppositories USP, 100 mg
Cures Most Vaginal Yeast Infections
Contains 7 Vaginal Suppositories
Drug Facts
Active ingredient (in each vaginal suppository) Purpose
Miconazole nitrate 100 mg.........................................................................................Vaginal antifungal
Use
• treats vaginal yeast infections
Warnings
For vaginal use only
Do not use if you have never had a vaginal yeast infection diagnosed by a doctor
Ask a doctor before use if you have
• vaginal itching and discomfort for the first time
• lower abdominal, back or shoulder pain, fever, chills, nausea, vomiting, or foul-smelling vaginal discharge
• vaginal yeast infections often (such as once a month or 3 in 6 months). You could be pregnant or have a serious underlying medical cause for your symptoms, including diabetes or a weakened immune system.
• been exposed to the human immunodeficiency virus (HIV) that causes AIDS
Ask a doctor or pharmacist before use if you are taking the prescription blood thinning medicine warfarin, because bleeding or bruising may occur.
When using this product
• do not use tampons, douches, spermicides, or other vaginal products. Condoms and diaphragms may be damaged by this product and fail to prevent pregnancy or sexually transmitted diseases (STDs).
• do not have vaginal intercourse
Stop use and ask a doctor if
• symptoms do not get better in 3 days
• symptoms last more than 7 days
• you get a rash, abdominal pain, fever, chills, nausea, vomiting, or foul-smelling vaginal discharge
If pregnant or breast-feeding, ask a health professional before use
Keep out of reach of children. If swallowed, get medical help or contact a Poison Control Center right away.
Directions
• before using this product, read the enclosed brochure for complete instructions
• adults and children 12 years of age and over:
• insert 1 suppository into the vagina at bedtime for 7 nights in a row • wash applicator after each use
• children under 12 years of age: ask a doctor
Drug Facts (continued)
Other information
• store at 15°-30°C (59°-86°F). Avoid heat over 30°C (86°F).
• do not use if suppository wrapper is missing or damaged (each suppository is individually wrapped)
Inactive ingredienthydrogenated vegetable oil base
Drug Facts (continued)
Questions? call 1-800-922-1038
Manufactured by: G&W Laboratories, Inc.
111 Coolidge Street
South Plainfield, NJ 07080
Visit our website @ www.gwlabs.com

Repackaged by: Rebel Distributors Corp.
3607 Old Conejo Rd.
Thousand Oaks, CA 91320

TAMPER-EVIDENT: For your safety each suppository is individually wrapped. If a suppository is unwrapped or there are signs of tampering, DO NOT USE.